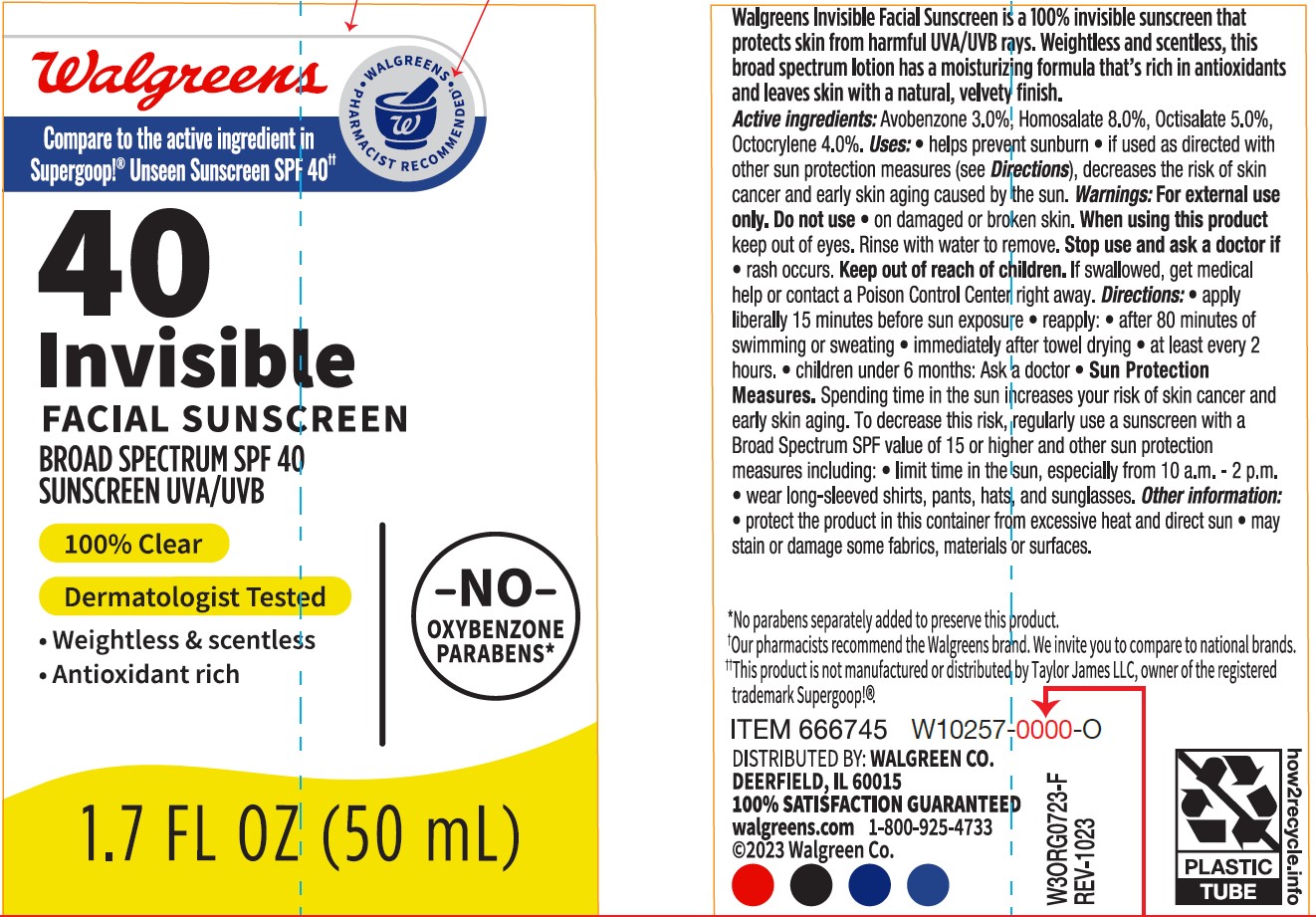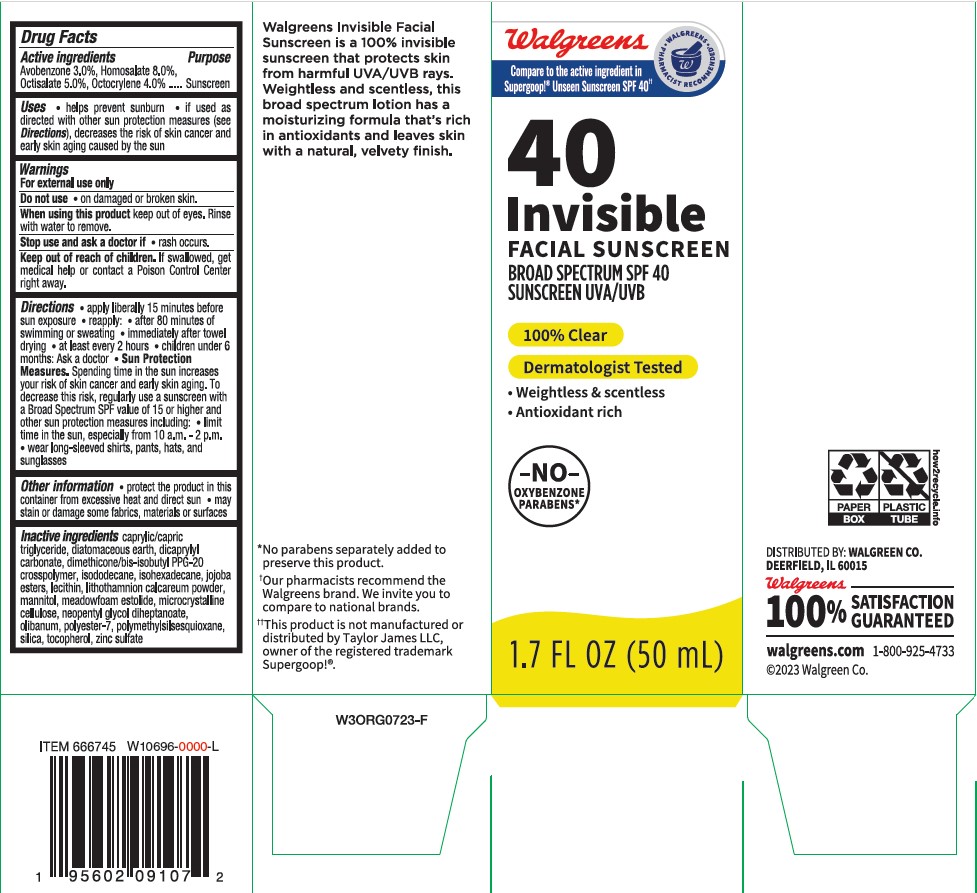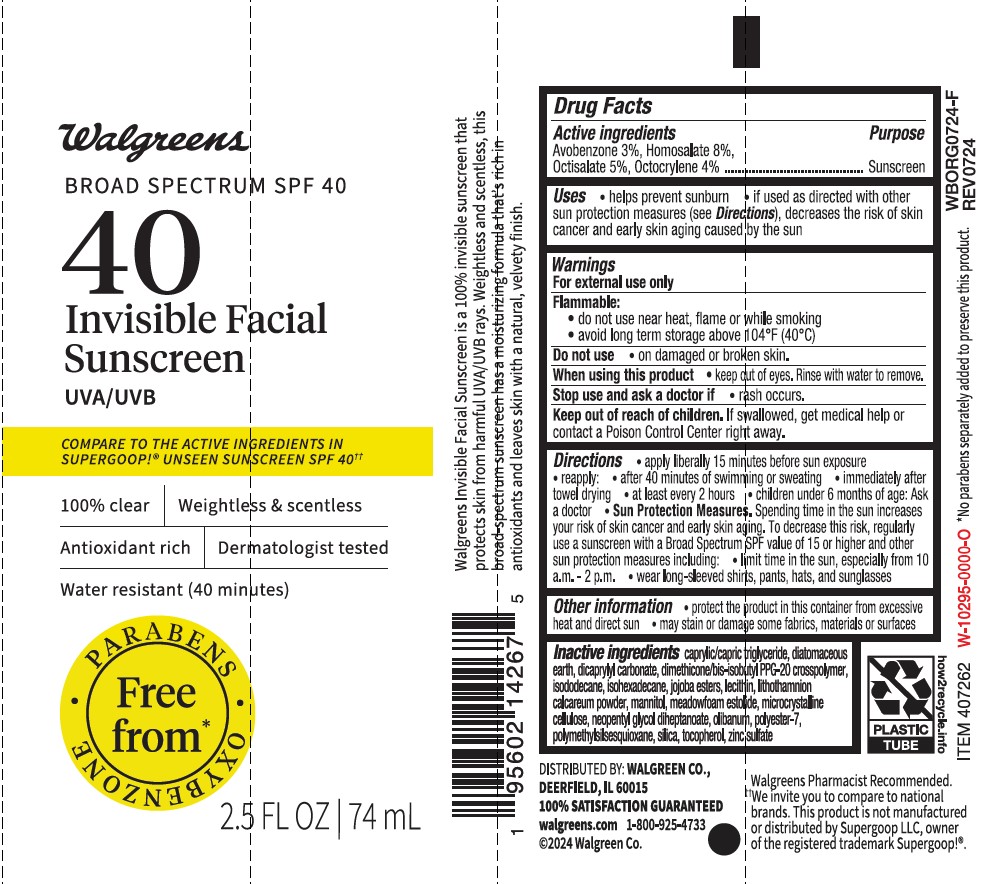 DRUG LABEL: Walgreens 40 Invisible Facial Sunscreen Broad Spectrum SPF 40
NDC: 0363-0349 | Form: GEL
Manufacturer: WALGREEN COMPANY
Category: otc | Type: HUMAN OTC DRUG LABEL
Date: 20241009

ACTIVE INGREDIENTS: HOMOSALATE 80 mg/1 mL; AVOBENZONE 30 mg/1 mL; OCTISALATE 50 mg/1 mL; OCTOCRYLENE 40 mg/1 mL
INACTIVE INGREDIENTS: DIMETHICONE/BIS-ISOBUTYL PPG-20 CROSSPOLYMER; ISOHEXADECANE; ISODODECANE; POLYESTER-7; LECITHIN, SOYBEAN; POLYMETHYLSILSESQUIOXANE (4.5 MICRONS); .ALPHA.-TOCOPHEROL, DL-; SILICON DIOXIDE; NEOPENTYL GLYCOL DIETHYLHEXANOATE; HYDROGENATED JOJOBA OIL, RANDOMIZED; BOSWELLIA SERRATA RESIN OIL; DIATOMACEOUS EARTH; DICAPRYLYL CARBONATE; MEDIUM-CHAIN TRIGLYCERIDES; PHYMATOLITHON CALCAREUM; MEADOWFOAM ESTOLIDE; ZINC SULFATE ANHYDROUS; MICROCRYSTALLINE CELLULOSE; MANNITOL

Walgreens 40 Invisible Facial Sunscreen Broad Spectrum

Active ingredients

Avobenzone 3.0%, Homosalate 8.0%, Octisalate 5.0%, Octocrylene 4.0%

Purpose

Sunscreen

Uses

- Helps prevent sunburn
- If used as directed with other sun protection measures (see Directions), decreases the risk of skin cancer and early aging caused by the sun

Warnings

For external use only

Do not use

• on damaged or broken skin.

When using this product

keep out of eyes. Rinse with water to remove.

Stop use and ask a doctor if

• rash occurs.

Keep out of reach of children.

If swallowed, get medical help or contact a Poison Control Center right away.

Directions

- apply liberally 15 minutes before sun exposure.
- reapply:
- after 80 minutes of swimming or sweating
- immediately after towel drying
- at least every 2 hours
- children under 6 months of age: Ask a doctor
- Sun Protection Measures. Spending time in the sun increases your risk of skin cancer and early skin aging. To decrease this risk, regularly use a sunscreen with a Broad Spectrum SPF value of 15 or higher and other sun protection measures including:
- limit time in the sun especially from 10 a.m. – 2 p.m.
- wear long-sleeved shirts, pants, hats, and sunglasses

Other information

- protect the product in this container from excessive heat and direct sun
- may stain or damage some fabrics, materials or surfaces

Inactive ingredients

dimethicone/bis-isobutyl PPG-20 crosspolymer, isododecane, caprylic/capric triglyceride, microcrystalline cellulose, isohexadecane, tocopherol, dicaprylyl carbonate, lithothamnion calcareum powder, meadowfoam estolide, olibanum, jojoba esters, lecithin, neopentyl glycol diheptanoate, polyester-7, silica, polymethylsilsesquioxane, mannitol, diatomaceous earth, zinc sulfate